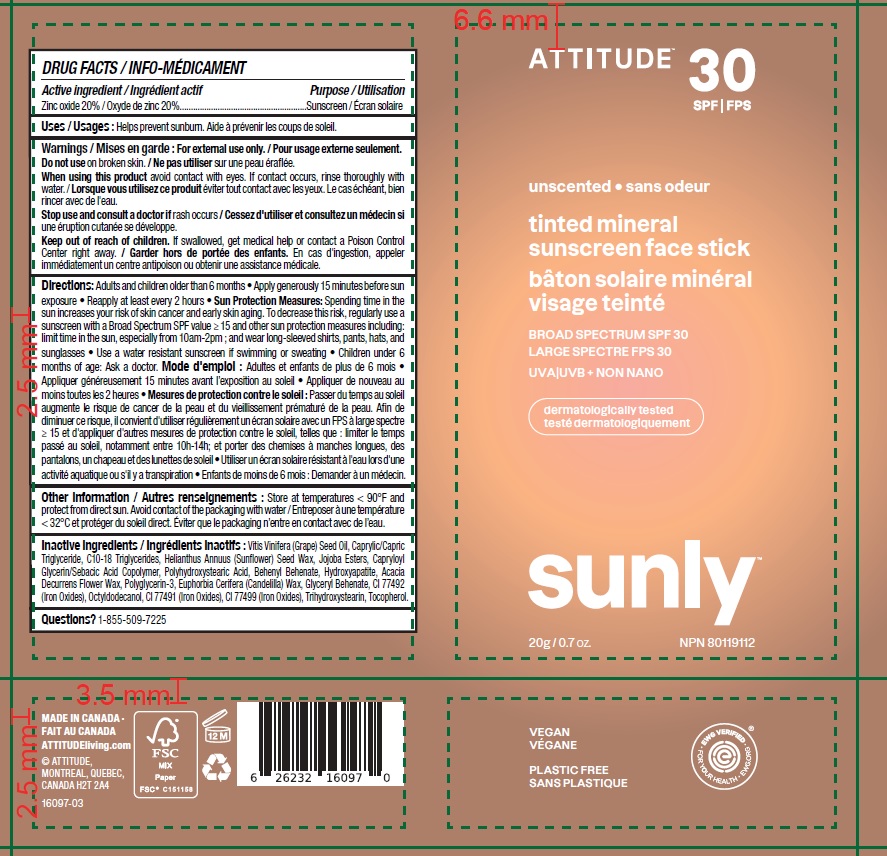 DRUG LABEL: ATTITUDE Sunly Tinted Mineral Sunscreen Face Stick Unscented SPF 30
NDC: 61649-097 | Form: STICK
Manufacturer: 9055-7588 Quebec Inc. DBA Attitude
Category: otc | Type: HUMAN OTC DRUG LABEL
Date: 20250113

ACTIVE INGREDIENTS: ZINC OXIDE 20 g/100 g
INACTIVE INGREDIENTS: HELIANTHUS ANNUUS SEED WAX; .ALPHA.-TOCOPHEROL; MEDIUM-CHAIN TRIGLYCERIDES; GRAPE SEED OIL; POLYHYDROXYSTEARIC ACID (2300 MW); ACACIA DECURRENS FLOWER WAX; TRIBASIC CALCIUM PHOSPHATE; FERRIC OXIDE YELLOW; BEHENYL BEHENATE; OCTYLDODECANOL; JOJOBA OIL; C10-18 TRIGLYCERIDES; CAPRYLOYL GLYCERIN/SEBACIC ACID COPOLYMER (2000 MPA.S); CANDELILLA WAX; FERRIC OXIDE RED; FERROSOFERRIC OXIDE; POLYGLYCERIN-3; GLYCERYL MONOBEHENATE; TRIHYDROXYSTEARIN

ATTITUDE Sunly Tinted Mineral Sunscreen Face Stick - Unscented - SPF 30

DRUG FACTS

ACTIVE INGREDIENT

Zinc oxide (20 %)

PURPOSE

Sunscreen

INDICATIONS AND USAGE

Helps prevent sunburn.

WARNINGS

For external use only.

Do not use on broken skin.

When using this product avoid contact with eyes. If contact occurs, rinse thoroughly with water.

Keep out of reach of children. If swallowed, get medical help or contact a Poison Control Center right away.

Stop use and consult a doctor if rash occurs.

DOSAGE AND ADMINISTRATION

Adults and children older than 6 months.

- Apply generously 15 minutes before sun exposure.
- Reapply at least every 2 hours.
- Sun Protection Measures: Spending time in the sun increases your risk of skin cancer and early aging. To decrease this risk, regularly use a sunscreen with a Broad Spectrum SPFvalue of 15 or higher and other sun protection measures including: limit time in the sun, especially from 10am-2pm; and wear long-sleeved shirts, pants, hats and sunglasses.
- Use a water resistant sunscreen if swimming or sweating.
- Children under 6 months of age: Ask a doctor.

STORAGE AND HANDLING

Store at temperatures < 90F and protect from direct sun. Avoid contact of packaging with water.

INACTIVE INGREDIENT

Vitis Vinifera (Grape) Seed Oil, Caprylic/Capric Triglyceride, C10-18 Triglycerides, Helianthus Annuus (Sunflower) Seed Wax, Jojoba Esters, Capryloyl Glycerin/Sebacic Acid Copolymer, Polyhydroxystearic Acid, Behenyl Behenate, Hydroxyapatite, Acacia Decurrens Flower Wax, Polyglycerin-3, Euphorbia Cerifera (Candelilla) Wax, Glyceryl Behenate, CI 77492 (Iron Oxides), Octyldodecanol, CI 77491 (Iron Oxides), CI 77499 (Iron Oxides), Trihydroxystearin, Tocopherol.

Questions ? 1-855-509-7225

PACKAGE LABEL

ATTITUDE

SPF 30

unscented

tinted mineral sunscreen face stick

BROAD SPECTRUM SPF 30

UVA UVB + NON NANO

Kids

SUNLY Plastic Free Suncare

20 g / 0.7 oz.

NPN 80119112

Vegan

Plastic Free

EWG Verified

Dermatologically tested